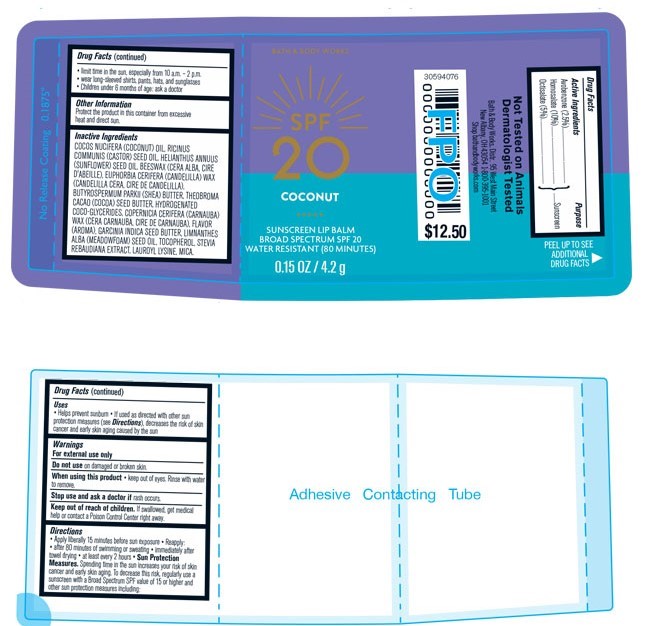 DRUG LABEL: Bath and Body Works SPF20 Coconut Lip Balm
NDC: 51514-0360 | Form: STICK
Manufacturer: Autumn Harp
Category: otc | Type: HUMAN OTC DRUG LABEL
Date: 20230224

ACTIVE INGREDIENTS: OCTISALATE 5 mg/100 mg; AVOBENZONE 2.5 mg/100 mg; HOMOSALATE 10 mg/100 mg
INACTIVE INGREDIENTS: SYNTHETIC BEESWAX; SHEA BUTTER; COCOA BUTTER; HYDROGENATED COCO-GLYCERIDES; MEADOWFOAM SEED OIL; TOCOPHEROL; STEVIA LEAF; BENZYL ALCOHOL; LAUROYL LYSINE; BENZYL BENZOATE; CARNAUBA WAX; MICA; COCONUT OIL; CANDELILLA WAX; GARCINIA INDICA SEED BUTTER; CASTOR OIL; SUNFLOWER OIL; MEDIUM-CHAIN TRIGLYCERIDES; SOYBEAN OIL

Bath and Body Works SPF20 Coconut Sunscreen Lip Balm

Drug Facts

Active Ingredient

Avobenzone 2.5%

Homosolate 10%

Octisalate 5%

Purpose

Sunscreen

Uses

- Helps prevent sunburn
- If used as directed with other sun protection measures (see Directions), decreases the risk of skin cancer and early skin aging caused by the sun.

Warnings

For external use only

Do not use on damaged or broken skin

When using this product

- keep out of eyes. Rinse with water to remove.

Stop use and ask a doctor if rash occurs.

Keep out of reach of children. If swallowed get medical help or conatct a Poison Control Center right away.

Directions

- Apply liberally 15 minutes before sun exposure
- Reapply:
- after 80 minutes of swimming or sweating
- Immediately after towel drying
- at least every 2 hours
- Sun Protection Measures

Spending time in the sun increases your risk of skin cancer and early skin aging. To decrease this risk, regularly use a sunscreen with a Broad Spectrum SPF value of 15 or higher and other sun protection meansures including:

- limit time in the sun, especially from 10 am - 2 pm
- wear long-sleeved shirts, pants, hats and sunglasses
- Children under 6 months of age: ask a doctor

Other Information

Protect the product in this container from excessive heat and direct sun.

Inactive Ingredients

Cocous nucifera (coconut) oil, Ricinus communis (Castor) seed oil, Helianthus annuus (Sunflower) seed oil, Beeswax (cera alba, cire l'abeille), Euphorbia cerifera (candelilla) wax (candelilla cera, cire de candelilla), Butyrospermum parkii (Shea) butter, Hydrogenated coco-glycerides, Copernicia cerifera (carnauba) wax (cera carnauba, cire de carnauba), flavor (aroma), Garcinia indica seed butter, Limnathes alba (meadowfoarm) seed oil, Tocopherol, Stevia rebaudiana extract, Lauroyl lysine, Mica.